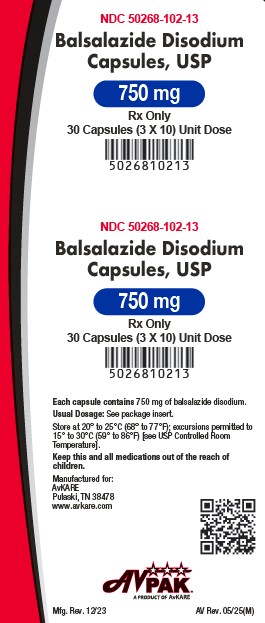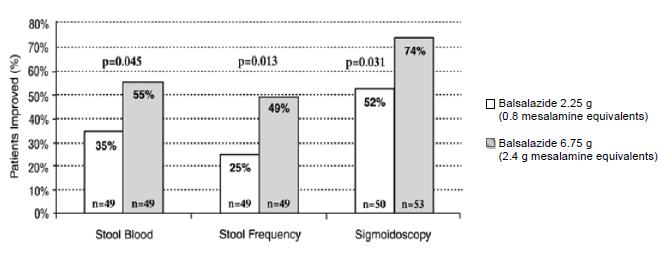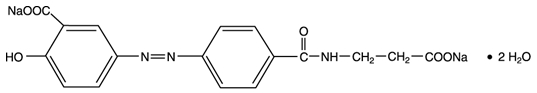 DRUG LABEL: Balsalazide Disodium
NDC: 50268-102 | Form: CAPSULE
Manufacturer: AvPAK
Category: prescription | Type: HUMAN PRESCRIPTION DRUG LABEL
Date: 20251230

ACTIVE INGREDIENTS: BALSALAZIDE DISODIUM 750 mg/1 1
INACTIVE INGREDIENTS: SILICON DIOXIDE; MAGNESIUM STEARATE; TITANIUM DIOXIDE; PROPYLENE GLYCOL; AMMONIA; SHELLAC; FERRIC OXIDE RED

HIGHLIGHTS OF PRESCRIBING INFORMATION

Balsalazide Disodium Capsules, USP
These highlights do not include all the information needed to use BALSALAZIDE DISODIUM CAPSULES safely and effectively. See full prescribing information for BALSALAZIDE DISODIUM CAPSULES.
BALSALAZIDE DISODIUM capsules, for oral administration
Initial U.S. Approval: 2000

1 INDICATIONS AND USAGE

- Balsalazide is a locally acting aminosalicylate indicated for the treatment of mildly to moderately active ulcerative colitis in patients 5 years of age and older. (1)
- Safety and effectiveness of balsalazide beyond 8 weeks in children (ages 5 to 17 years) and 12 weeks in adults have not been established. (1)

2 DOSAGE AND ADMINISTRATION

- Adult dose is three 750 mg balsalazide disodium capsules 3 times a day (6.75 g/day) with or without food for 8 weeks. Some adult patients required treatment for up to 12 weeks. (2.1)
- Pediatric dose is EITHER: (2.2, 8.4)

1. Three 750 mg balsalazide disodium capsules 3 times a day (6.75 g/day) with or without food for 8 weeks. OR:

2. One 750 mg balsalazide disodium capsule 3 times a day (2.25 g/day) with or without food for up to 8 weeks. Capsules may be swallowed whole or may be opened and sprinkled on applesauce, then chewed or swallowed immediately. (2.3, 12.3)

3 DOSAGE FORMS AND STRENGTHS

Capsules: 750 mg (3)

4 CONTRAINDICATIONS

Known or suspected hypersensitivity to salicylates, aminosalicylates, or any of the components of balsalazide disodium capsules or balsalazide metabolites. (4, 5.3)

5 WARNINGS AND PRECAUTIONS

Renal Impairment: Assess renal function at the beginning of treatment and periodically during treatment. Evaluate the risks and benefits in patients with known renal impairment or taking nephrotoxic drugs; monitor renal function. Discontinue if renal function deteriorates. (5.1, 7.1, 8.6)
Mesalamine-Induced Acute Intolerance Syndrome: Symptoms may be difficult to distinguish from an exacerbation of ulcerative colitis; monitor for worsening symptoms; discontinue treatment if acute intolerance syndrome is suspected. (5.2)
Hypersensitivity Reactions, including Myocarditis and Pericarditis: Evaluate patients immediately and discontinue if a hypersensitivity reaction is suspected. (5.3)
Hepatic Failure: Evaluate the risks and benefits in patients with known liver impairment. (5.4)
Severe Cutaneous Adverse Reactions: Discontinue at the first signs or symptoms of severe cutaneous adverse reactions or other signs of hypersensitivity and consider further evaluation (5.5)
Upper Gastrointestinal Tract Obstruction: Avoid in patients with pyloric stenosis or other organic or functional obstruction. (5.6)
Photosensitivity: Advise patients with pre-existing skin conditions to avoid sun exposure, wear protective clothing, and use a broad-spectrum sunscreen when outdoors. (5.7)
Nephrolithiasis: Stones containing mesalamine, the active moiety in balsalazide disodium capsules, are undetectable by standard radiography or computed tomography (CT). Ensure adequate fluid intake during treatment with balsalazide disodium capsules (5.8)
Interference with Laboratory Tests: Use of mesalamine may lead to spuriously elevated test results when measuring urinary normetanephrine by liquid chromatography with electrochemical detection. (5.9)

6 ADVERSE REACTIONS

Most common adverse reactions (incidence ≥3%) are headache, abdominal pain, diarrhea, nausea, vomiting, respiratory infection, and arthralgia. Adverse reactions in children were similar. (6.1)

To report SUSPECTED ADVERSE REACTIONS, contact AvKARE at 1-855-361-3993 or FDA at 1-800-FDA-1088 orwww.fda.gov/medwatch.

7 DRUG INTERACTIONS

In an in vitro study using human liver microsomes, balsalazide and its metabolites were not shown to inhibit the major CYP enzymes evaluated (CYP1A2, CYP2C9, CYP2C19, CYP2D6, and CYP3A4/5). (7)

8 USE IN SPECIFIC POPULATIONS

Renal impairment: Use balsalazide with caution in patients with a history of renal disease. (5.3)

FULL PRESCRIBING INFORMATION

1 INDICATIONS AND USAGE

Balsalazide disodium capsules are indicated for the treatment of mildly to moderately active ulcerative colitis in patients 5 years of age and older.

Limitations of Use
Safety and effectiveness of balsalazide beyond 8 weeks in pediatric patients 5 years to 17 years of age and 12 weeks in adults have not been established.

2 DOSAGE AND ADMINISTRATION

2.1 Important Preparation and Administration Instructions

• Evaluate renal function before initiating therapy with balsalazide disodium capsules [see Warnings and Precaution (5.1)].
• Swallow balsalazide disodium capsules whole. Do not cut, break, crush or chew the capsules.
• For patients who cannot swallow intact capsules, balsalazide disodium capsules may also be administered by opening the capsule and sprinkling the capsule contents on applesauce. If the capsules are opened for sprinkling, color variation of the powder inside the capsules ranges from orange to yellow and is expected due to color variation of the active pharmaceutical ingredient.
• Place a small amount (approximately 10 mL) of applesauce into a clean container.
• Carefully open the capsules.
• Sprinkle the capsule contents on the applesauce.
• Mix the capsule contents with the applesauce. The contents may be chewed, if necessary.
• Consume the entire amount of applesauce mixture immediately. Do not store the applesauce mixture for future use.
• Teeth and/or tongue staining may occur in some patients when administered sprinkled on applesauce.
• Drink an adequate amount of fluids [see Warnings and Precautions (5.8)].
• Take balsalazide disodium capsules with or without food [see Clinical Pharmacology (12.3)].

2.2 Recommended Dosage in Adults and Pediatric Patients 5 Years to 17 Years of Age

Adults
The recommended dosage in adults is 2.25 g (three 750 mg capsules) three times daily for up to 8 weeks. Some patients in the adult clinical trials required treatment for up to 12 weeks.

Pediatric Patients 5 Years to 17 Years of Age
The recommended dosage in pediatric patients 5 years to 17 years of age is either:

- 2.25 g (three 750 mg capsules) three times daily for up to 8 weeks;

OR:

- 750 mg (one capsule) three times daily for up to 8 weeks.

Use of balsalazide in the pediatric population for more than 8 weeks has not been evaluated in clinical trials [see Clinical Studies (14)].

3 DOSAGE FORMS AND STRENGTHS

Balsalazide disodium capsules, USP are available as opaque white capsules containing 750 mg balsalazide disodium, imprinted with “APO B750” in red ink.

4 CONTRAINDICATIONS

Balsalazide disodium capsules is contraindicated in patients with known or suspected hypersensitivity to salicylates, aminosalicylates, or to any of the components of balsalazide disodium capsules or balsalazide metabolites [see Warnings and Precautions (5.3), Adverse Reactions (6.2), Description (11)].

5 WARNINGS AND PRECAUTIONS

5.1 Renal Impairment

Renal impairment, including minimal change disease, acute and chronic interstitial nephritis, and renal failure, has been reported in patients given products such as balsalazide disodium capsules that release mesalamine into the gastrointestinal tract. Evaluate renal function prior to initiation of balsalazide disodium capsules and periodically while on therapy. Evaluate the risks and benefits of using balsalazide disodium capsules in patients with known renal impairment, a history of renal disease or taking nephrotoxic drugs. Discontinue balsalazide disodium capsules if renal function deteriorates while on therapy [see Drug Interactions (7.1), Use in Specific Populations (8.6)].

5.2 Mesalamine-Induced Acute Intolerance Syndrome

Balsalazide is converted to mesalamine, which has been associated with an acute intolerance syndrome that may be difficult to distinguish from an exacerbation of ulcerative colitis. Although the exact frequency of occurrence has not been determined, it has occurred in 3% of patients in controlled clinical trials of mesalamine or sulfasalazine. Symptoms include cramping, acute abdominal pain and bloody diarrhea, sometimes fever, headache, and rash. Monitor patients for worsening of these symptoms while on treatment. If acute intolerance syndrome is suspected, promptly discontinue treatment with balsalazide disodium capsules.

5.3 Hypersensitivity Reactions

Some patients have experienced a hypersensitivity reaction to sulfasalazine may have a similar reaction to balsalazide disodium capsules or to other compounds that contain or are converted to mesalamine.

Mesalamine-induced hypersensitivity reactions may present as internal organ involvement, including myocarditis, pericarditis, nephritis, hepatitis, pneumonitis and hematologic abnormalities. Evaluate patients immediately if signs or symptoms of a hypersensitivity reaction are present. Discontinue balsalazide disodium capsules if an alternative etiology for the signs and symptoms cannot be established.

5.4 Hepatic Failure

There have been reports of hepatic failure in patients with pre-existing liver disease who have been administered mesalamine. Because balsalazide is converted to mesalamine, evaluate the risks and benefits of using balsalazide disodium capsules in patients with known liver impairment.

5.5 Severe Cutaneous Adverse Reactions

Severe cutaneous adverse reactions, including Stevens-Johnson syndrome (SJS) and toxic epidermal necrolysis (TEN), drug reaction with eosinophilia and systemic symptoms (DRESS), and acute generalized exanthematous pustulosis (AGEP) have been reported with the use of mesalamine, the active moiety of balsalazide disodium capsules [see Adverse Reactions (6.2)]. Discontinue balsalazide disodium capsules at the first signs or symptoms of severe cutaneous adverse reactions or other signs of hypersensitivity and consider further evaluation.

5.6 Upper Gastrointestinal Tract Obstruction

Pyloric stenosis or other organic or functional obstruction in the upper gastrointestinal tract may cause prolonged gastric retention of balsalazide disodium capsules, which would delay mesalamine release in the colon. Avoid balsalazide disodium capsules in patients at risk of upper gastrointestinal tract obstruction.

5.7 Photosensitivity

Patients with pre-existing skin conditions such as atopic dermatitis and atopic eczema have reported more severe photosensitivity reactions. Advise patients to avoid sun exposure, wear protective clothing, and use a broad-spectrum sunscreen when outdoors.

5.8 Nephrolithiasis

Cases of nephrolithiasis have been reported with the use of mesalamine, the active moiety of balsalazide disodium capsules, including stones with 100% mesalamine content. Mesalamine-containing stones are radiotransparent and undetectable by standard radiography or computed tomography (CT). Ensure adequate fluid intake during treatment with balsalazide disodium capsules.

5.9 Interference with Laboratory Tests

Use of balsalazide disodium capsules, which is converted to mesalamine, may lead to spuriously elevated test results when measuring urinary normetanephrine by liquid chromatography with electrochemical detection because of the similarity in the chromatograms of normetanephrine and the main metabolite of mesalamine, N-acetyl-5-aminosalicylic acid (N-Ac-5-ASA). Consider an alternative, selective assay for normetanephrine.

6 ADVERSE REACTIONS

The following clinically significant adverse reactions are described elsewhere in labeling:

- Renal Impairment [see Warnings and Precautions (5.1)]
- Mesalamine-Induced Acute Intolerance Syndrome [see Warnings and Precautions (5.2)]
- Hypersensitivity Reactions [see Warnings and Precautions (5.3)]
- Hepatic Failure [see Warnings and Precautions (5.4)]
- Severe Cutaneous Adverse Reactions [see Warnings and Precautions (5.5)]
- Upper Gastrointestinal Tract Obstruction [see Warnings and Precautions (5.6)]
- Photosensitivity [see Warnings and Precautions (5.7)]
- Nephrolithiasis [see Warnings and Precautions (5.8)]

6.1 Clinical Studies Experience

Because clinical studies are conducted under widely varying conditions, adverse reaction rates observed in the clinical studies of a drug cannot be directly compared to rates in the clinical studies of another drug and may not reflect the rates observed in practice.

Adult Ulcerative Colitis
During clinical development, 259 adult patients with active ulcerative colitis were exposed to 6.75 g/day balsalazide in 4 controlled trials.

In the 4 controlled clinical trials patients receiving a balsalazide dose of 6.75 g/day most frequently reported the following adverse reactions: headache (8%), abdominal pain (6%), diarrhea (5%), nausea (5%), vomiting (4%), respiratory infection (4%), and arthralgia (4%). Withdrawal from therapy due to adverse reactions was comparable among patients on balsalazide and placebo.

Adverse reactions reported by 1% or more of patients who participated in the 4 well-controlled, Phase 3 trials are presented by treatment group (Table 1).

The number of placebo patients (35), however, is too small for valid comparisons. Some adverse reactions, such as abdominal pain, fatigue, and nausea were reported more frequently in women than in men. Abdominal pain, rectal bleeding, and anemia can be part of the clinical presentation of ulcerative colitis.

Table 1: Adverse Reactions Occurring in ≥ 1 % of Adult Balsalazide Patients in Controlled Trials*

Adverse Reaction | Balsalazide Capsules 6.75 g/day [N=259] | Placebo [N=35]
Abdominal pain Diarrhea Arthralgia Rhinitis Insomnia Fatigue Flatulence Fever Dyspepsia Pharyngitis Coughing Anorexia Urinary tract infection Myalgia Flu-like disorder Dry mouth Cramps Constipation | 16 (6%) 14 (5%) 9 (4%) 6 (2%) 6 (2%) 6 (2%) 5 (2%) 5 (2%) 5 (2%) 4 (2%) 4 (2%) 4 (2%) 3 (1%) 3 (1%) 3 (1%) 3 (1%) 3 (1%) 3 (1%) | 1 (3%) 1 (3%) 0% 0% 0% 0% 0% 0% 0% 0% 0% 0% 0% 0% 0% 0% 0% 0%

*Adverse reactions occurring in at least 1 % of balsalazide Patients which were less frequent than placebo for the same event were not included in the table.

Pediatric Ulcerative Colitis
In a clinical trial in 68 pediatric patients aged 5 to 17 years with mildly to moderately active ulcerative colitis who received 6.75 g/day or 2.25 g/day balsalazide disodium for 8 weeks, the most frequently reported adverse reactions were headache (15%), abdominal pain upper (13%), abdominal pain (12%), vomiting (10%), diarrhea (9%), colitis ulcerative (6%), nasopharyngitis (6%), and pyrexia (6%). [see Table 2]

One patient who received balsalazide disodium 6.75 g/day and 3 patients who received balsalazide disodium 2.25 g/day discontinued treatment because of adverse reactions. In addition, 2 patients in each dose group discontinued because of a lack of efficacy.

Adverse reactions reported by 3% or more of pediatric patients within either treatment group in the Phase 3 trial are presented in Table 2.

Table 2: Treatment-Emergent Adverse Reactions Reported by ≥3% of Patients in Either Treatment Group in a Controlled Study of 68 Pediatric Patients

 | balsalazide disodium
Adverse Reaction | 6.75 g/day [N=33] | 2.25 g/day [N=35] | Total [N=68]
Headache | 5 (15%) | 5 (14%) | 10 (15%)
Abdominal pain upper | 3 (9%) | 6 (17%) | 9 (13%)
Abdominal pain | 4 (12%) | 4 (11%) | 8 (12%)
Vomiting | 1 (3%) | 6 (17%) | 7 (10%)
Diarrhea | 2 (6%) | 4 (11%) | 6 (9%)
Colitis ulcerative | 2 (6%) | 2 (6%) | 4 (6%)
Nasopharyngitis | 3 (9%) | 1 (3%) | 4 (6%)
Pyrexia | 0 (0%) | 4 (11%) | 4 (6%)
Hematochezia | 0 (0%) | 3 (9%) | 3 (4%)
Nausea | 0 (0%) | 3 (9%) | 3 (4%)
Influenza | 1 (3%) | 2 (6%) | 3 (4%)
Fatigue | 2 (6%) | 1 (3%) | 3 (4%)
Stomatitis | 0 (0%) | 2 (6%) | 2 (3%)
Cough | 0 (0%) | 2 (6%) | 2 (3%)
Pharyngolaryngeal pain | 2 (6%) | 0 (0%) | 2 (3%)
Dysmenorrhea | 2 (6%) | 0 (0%) | 2 (3%)

6.2 Postmarketing Experience

The following adverse reactions have been identified during post-approval use of balsalazide, or other products which contain or are metabolized to mesalamine. Because these reactions are reported voluntarily from a population of uncertain size, it is not always possible to reliably estimate their frequency or establish a causal relationship to drug exposure.
Cardiovascular and Vascular: Myocarditis, pericarditis, vasculitis [see Warnings and Precautions (5.3)]
Respiratory: pleural effusion, pneumonia (with and without eosinophilia), alveolitis, pleurisy/pleuritis
Renal: renal failure, interstitial nephritis, nephrolithiasis [see Warnings and Precautions (5.1, 5.8)]

- Urine discoloration occurring ex-vivo caused by contact of mesalamine, including inactive metabolite, with surfaces or water treated with hypochlorite-containing bleach

Gastrointestinal: pancreatitis
Dermatologic: pruritus, alopecia

Hepatic: hepatotoxicity, elevated liver function tests (SGOT/AST, SGPT/ALT, GGT, LDH, alkaline phosphatase, bilirubin), jaundice, cholestatic jaundice, cirrhosis, hepatocellular damage including liver necrosis and liver failure, Kawasaki-like syndrome including hepatic dysfunction
Skin: SJS/TEN, DRESS, and AGEP [see Warnings and Precautions (5.5)]

To report SUSPECTED ADVERSE REACTIONS, contact AvKARE at 1-855-361-3993; email drugsafety@avkare.com or FDA at 1-800-FDA-1088 or www.fda.gov/medwatch.

7 DRUG INTERACTIONS

7.1 Nephrotoxic Agents, Including Non-Steroidal Anti-Inflammatory Drugs
The concurrent use of mesalamine with known nephrotoxic agents, including non-steroidal anti-inflammatory drugs (NSAIDs), may increase the risk of renal reactions. Monitor patients taking nephrotoxic drugs for changes in renal function and mesalamine-related adverse reactions [see Warnings and Precautions (5.1)].

7.2 Azathioprine or 6-Mercaptopurine
The concurrent use of mesalamine with azathioprine or 6-mercaptopurine and/or any other drugs known to cause myelotoxicity may increase the risk for blood disorders, bone marrow failure, and associated complications. If concomitant use of balsalazide disodium capsules and azathioprine or 6-mercaptopurine cannot be avoided, monitor blood tests, including complete blood cell counts and platelet counts.

7.3 Interference With Urinary Normetanephrine Measurements
Use of balsalazide disodium capsules, which is converted to mesalamine, may lead to spuriously elevated test results when measuring urinary normetanephrine by liquid chromatography with electrochemical detection [see Warnings and Precautions (5.9)]. Consider an alternative, selective assay for normetanephrine.

8 USE IN SPECIFIC POPULATIONS

8.1 Pregnancy

Risk Summary
Published data from meta-analyses, cohort studies and case series on the use of mesalamine, the active moiety of balsalazide, during pregnancy have not reliably informed an association with mesalamine and major birth defects, miscarriage, or adverse maternal or fetal outcomes (see Data). There are adverse effects on maternal and fetal outcomes associated with ulcerative colitis in pregnancy (see Clinical Considerations). In animal reproduction studies, there were no adverse developmental effects observed after oral administration of balsalazide disodium in pregnant rats and rabbits during organogenesis at doses up to 2.4 and 4.7 times,
respectively, the maximum recommended human dose (MRHD) (see Data).

The estimated background risk of major birth defects and miscarriage for the indicated population is unknown. All pregnancies have a background risk of birth defect, loss, or other adverse outcomes. In the U.S. general population, the estimated background risk of major birth defects and miscarriage in clinically recognized pregnancies is 2% to 4% and 15% to 20%, respectively.

Clinical Considerations
Disease-associated maternal and embryo/fetal risk

Published data suggest that increased disease activity is associated with the risk of developing adverse pregnancy outcomes in women with ulcerative colitis. Adverse pregnancy outcomes include preterm delivery (before 37 weeks of gestation), low birth weight (less than 2,500 g) infants, and small for gestational age at birth.

Data
Human Data
Published data from meta-analyses, cohort studies and case series on the use of mesalamine, the active moiety of balsalazide, during early pregnancy (first trimester) and throughout pregnancy have not reliably informed an association of mesalamine and major birth defects, miscarriage, or adverse maternal or fetal outcomes. There is no clear evidence that mesalamine exposure in early pregnancy is associated with an increased risk in major congenital malformations, including cardiac malformations. Published epidemiologic studies have important methodological limitations which hinder interpretation of the data, including inability to control for confounders, such as underlying maternal disease, and maternal use of concomitant medications, and missing information on the dose and duration of use for mesalamine products.

Animal Data
Reproduction studies were performed in rats and rabbits following administration of balsalazide during organogenesis at oral doses up to 2 g/kg/day, 2.4 and 4.7 times the MRHD based on body surface area for the rat and rabbit, respectively, and revealed no adverse embryofetal developmental effects due to balsalazide disodium.

8.2 Lactation

Risk Summary
Data from published literature report the presence of mesalamine and its metabolite, N acetyl-5 aminosalicylic acid, in human milk in small amounts with relative infant doses (RID) of 0.1% or less for mesalamine (see Data). There are case reports of diarrhea in breastfed infants exposed to mesalamine (see Clinical Considerations). There is no information on the effects of the drug on milk production. The lack of clinical data during lactation precludes a clear determination of the risk of balsalazide to an infant during
lactation; therefore, the developmental and health benefits of breastfeeding should be considered along with the mother’s clinical need for balsalazide and any potential adverse effects on the breastfed child from balsalazide or from the underlying maternal condition.

Clinical Considerations
Advise the caregiver to monitor breastfed infants for diarrhea.

Data
In published lactation studies, maternal mesalamine doses from various oral and rectal mesalamine formulations and products ranged from 500 mg to 4.8 g daily. The average concentration of mesalamine in milk ranged from non-detectable to 0.5 mg/L. The average concentration of N-acetyl-5-aminosalicylic acid in milk ranged from 0.2 to 9.3 mg/L. Based on these concentrations, estimated infant daily dosages for an exclusively breastfed infant are 0 to 0.075 mg/kg/day (RID 0 to 0.1%) of mesalamine and 0.03 to 1.4 mg/kg/day of N-acetyl-5-aminosalicylic acid.

8.4 Pediatric Use

The safety and effectiveness of balsalazide disodium has been established for the treatment of mildly to moderately active ulcerative colitis in pediatric and adolescent patients 5 years to 17 years of age. Use of balsalazide disodium for this indication is supported by evidence from adequate and well-controlled clinical studies in adults with additional pharmacokinetic and safety data in pediatric patients aged 5 years to 17 years [see Adverse Reactions (6.1), Clinical Pharmacology (12.3), and Clinical Studies (14.2)].

Based on the limited data available, dosing can be initiated at either 6.75 or 2.25 g/day [see Dosage and Administration (2.2)].

The safety and effectiveness of balsalazide disodium capsules in pediatric patients below the age of 5 years have not been established.

8.5 Geriatric Use

Clinical trials of balsalazide disodium did not include sufficient numbers of subjects aged 65 years and over to determine whether they respond differently than younger subjects. Reports from uncontrolled clinical studies and postmarketing reporting systems suggested a higher incidence of blood dyscrasias, i.e., neutropenia and pancytopenia, in patients who were 65 years or older compared to younger patients taking mesalaminecontaining products. Balsalazide disodium is converted into mesalamine in the colon. Monitor complete blood cell counts and platelet counts in elderly patients during treatment with balsalazide disodium. In general, consider the greater frequency of decreased hepatic, renal, or cardiac function, and of concomitant disease or other drug therapy in elderly patients when prescribing balsalazide disodium capsules [see Use in Specific Populations (8.6)].

8.6 Renal Impairment

Mesalamine is known to be substantially excreted by the kidney, and the risk of adverse reactions to balsalazide disodium, which is converted to mesalamine, may be greater in patients with impaired renal function. Evaluate renal function in all patients prior to initiation and periodically while on balsalazide disodium capsules therapy. Monitor patients with known renal impairment or history of renal disease or taking nephrotoxic drugs for decreased renal function and mesalamine-related adverse reactions. Discontinue balsalazide disodium capsules if renal function deteriorates while on therapy [see Warnings and Precautions (5.1), Adverse Reactions (6.2), Drug Interactions (7.1)].

10 OVERDOSAGE

Balsalazide disodium capsules is an aminosalicylate, and symptoms of salicylate toxicity include: nausea, vomiting and abdominal pain, tachypnea, hyperpnea, tinnitus, and neurologic symptoms (headache, dizziness, confusion, seizures). Severe salicylate intoxication may lead to electrolyte and blood pH imbalance and potentially to other organ (e.g., renal and liver) damage. There is no specific antidote for balsalazide overdose; however, conventional therapy for salicylate toxicity may be beneficial in the event of acute overdosage and may include gastrointestinal tract decontamination to prevent further absorption. Proper medical care should be sought immediately with appropriate supportive care, including the possible use of emesis, cathartics, and activated charcoal to prevent further absorption. Correct fluid and electrolyte imbalance by the administration of appropriate intravenous therapy and maintain adequate renal function.

11 DESCRIPTION

Each balsalazide disodium capsule, USP contains 750 mg of balsalazide disodium, a prodrug that is enzymatically cleaved in the colon to produce mesalamine (5-aminosalicylic acid or 5-ASA), an anti-inflammatory drug. Each capsule of balsalazide (750 mg) is equivalent to 267 mg of mesalamine. Balsalazide disodium has the chemical name (E)-5-[[-4-[[(2- carboxyethyl)amino]carbonyl] phenyl]azo]-2-hydroxybenzoic acid, disodium salt, dihydrate. Its structural formula is:

Molecular Weight: 437.32

Molecular Formula: C17H13N3O6Na2•2H2O

Balsalazide disodium is a stable, odorless orange to yellow microcrystalline powder. It is freely soluble in water and isotonic saline, sparingly soluble in methanol and ethanol, and practically insoluble in all other organic solvents.

Inactive Ingredients: Each hard gelatin capsule contains colloidal silicon dioxide, magnesium stearate and titanium dioxide. The capsule imprinting ink contains propylene glycol, strong ammonia solution, shellac and red iron oxide. The sodium content of each capsule is approximately 86 mg.

12 CLINICAL PHARMACOLOGY

12.1 Mechanism of Action

Balsalazide disodium is delivered intact to the colon where it is cleaved by bacterial azoreduction to release equimolar quantities of mesalamine, which is the therapeutically active portion of the molecule, and the 4-aminobenzoyl-β-alanine carrier moiety. The carrier moiety released when balsalazide disodium is cleaved is only minimally absorbed and is largely inert.

The mechanism of action of 5-ASA is unknown, but appears to be local to the colonic mucosa rather than systemic. Mucosal production or arachidonic acid metabolites, both through the cyclooxygenase pathways, i.e., prostanoids, and through the lipoxygenase pathways, i.e., leukotrienes and hydroxyeicosatetraenoic acids, is increased in patients with chronic inflammatory bowel disease, and it is possible that 5-ASA diminishes inflammation by blocking production of arachidonic acid metabolites in the colon.

12.3 Pharmacokinetics

Balsalazide disodium capsules contain a powder of balsalazide disodium that is insoluble in acid and designed to be delivered to the colon as the intact prodrug. Upon reaching the colon, bacterial azoreductases cleave the compound to release 5-ASA, the therapeutically active portion of the molecule, and 4-aminobenzoyl-β-alanine. The 5-ASA is further metabolized to yield Nacetyl-5-aminosalicylic acid (N-Ac-5-ASA), a second key metabolite.

Absorption

The plasma pharmacokinetics of balsalazide and its key metabolites from a crossover study in healthy volunteers are summarized in Table 3. In this study, a single oral dose of balsalazide 2.25 g was administered to healthy volunteers as intact capsules (3 x 750 mg) under fasting conditions, as intact capsules (3 x 750 mg) after a high-fat meal, and unencapsulated (3 x 750 mg) as sprinkles on applesauce.

Effect of Food
The plasma pharmacokinetics of balsalazide and its key metabolites from a crossover study in healthy subjects are summarized in Table 3. In this study, a single oral dose of balsalazide 2.25 g was administered to healthy volunteers as intact capsules (3 x 750 mg) under fasting conditions, as intact capsules (3 x 750 mg) after a high-fat meal, and unencapsulated (3 x 750 mg) as sprinkles on applesauce.

Table 3: Plasma Pharmacokinetics for Balsalazide and Key Metabolites (5-ASA and N-Ac-5-ASA) with Administration of Balsalazide Following a Fast, a High-Fat Meal, and Drug Contents Sprinkled on Applesauce (Mean ± SD)
 | Fasting; n = 17 | High-Fat Meal; n = 17 | Sprinkled; n = 17
Cmax (mcg/mL)
Balsalazide | 0.51 ± 0.32 | 0.45 ± 0.39 | 0.21 ± 0.12
5-ASA | 0.22 ± 0.12 | 0.11 ± 0.136 | 0.29 ± 0.17
N-Ac-5-ASA | 0.88 ± 0.39 | 0.64 ± 0.534 | 1.04 ± 0.57
AUClast mcg·hr/mL)
Balsalazide | 1.35 ± 0.73 | 1.52 ± 1.01 | 0.87 ± 0.48
5-ASA | 2.59 ± 1.46 | 2.10 ± 2.58 | 2.99 ± 1.70
N-Ac-5-ASA | 17.8 ± 8.14 | 17.7 ± 13.7 | 20.0 ± 11.4
Tmax (h)
Balsalazide | 0.8 ± 0.85 | 1.2 ± 1.11 | 1.6 ± 0.44
5-ASA | 8.2 ± 1.98 | 22.0 ± 8.23 | 8.7 ± 1.99
N-Ac-5-ASA | 9.9 ± 2.49 | 20.2 ± 8.94 | 10.8 ± 5.39

A relatively low systemic exposure was observed under all three administered conditions (fasting, fed with high-fat meal, sprinkled on applesauce), which reflects the variable, but minimal absorption of balsalazide disodium and its metabolites. The data indicate that both Cmax and AUClast were lower, while tmax was markedly prolonged, under fed (high-fat meal) compared to fasted conditions. Moreover, the data suggest that dosing balsalazide disodium as a sprinkle or as a capsule provides highly variable, but relatively similar mean pharmacokinetic parameter values. No inference can be made as to how the systemic exposure differences of balsalazide and its metabolites in this study might predict the clinical efficacy under different dosing conditions (i.e., fasted, fed with high-fat meal, or sprinkled on applesauce) since clinical efficacy after balsalazide disodium administration is presumed to be primarily due to the local effects of 5- ASA on the colonic mucosa.

In a separate study of adult patients with ulcerative colitis, who received balsalazide, 1.5 g twice daily, for over 1 year, systemic drug exposure, based on mean AUC values, was up to 60 times greater (0.008 mcg•hr/mL to 0.480 mcg•hr/mL) when compared to that obtained in healthy subjects who received the same dose.

Distribution

The binding of balsalazide to human plasma proteins was ≥99%.

Elimination
Metabolism
The products of the azoreduction of this compound, 5-ASA and 4-aminobenzoyl-β-alanine, and their N-acetylated metabolites have been identified in plasma, urine and feces.

Excretion
Following single-dose administration of 2.25 g balsalazide (three 750 mg capsules) under fasting conditions in healthy subjects, mean urinary recovery of balsalazide, 5-ASA, and N-Ac-5-ASA was 0.20%, 0.22% and 10.2%, respectively.

In a multiple-dose study in healthy subjects receiving a balsalazide dose of two 750 mg capsules twice daily (3 g/day) for 10 days, mean urinary recovery of balsalazide, 5-ASA, and N-Ac-5-ASA was 0.1%, 0%, and 11.3%, respectively. During this study, subjects received their morning dose 0.5 hours after being fed a standard meal, and subjects received their evening dose 2 hours after being fed a standard meal.

In a study with 10 healthy volunteers, 65% of a single 2.25-gram dose of balsalazide was recovered as 5-ASA, 4-aminobenzoyl-β-alanine, and the N-acetylated metabolites in feces, while <1% of the dose was recovered as parent compound.

In a study that examined the disposition of balsalazide in patients who were taking 3 to 6 g of balsalazide daily for more than 1 year and who were in remission from ulcerative colitis, less than 1% of an oral dose was recovered as intact balsalazide in the urine. Less than 4% of the dose was recovered as 5-ASA, while virtually no 4-aminobenzoyl-β-alanine was detected in urine. The mean urinary recovery of N-Ac-5-ASA and N-acetyl-4-aminobenzoyl-β-alanine comprised <16% and <12% of the balsalazide dose, respectively. No fecal recovery studies were performed in this population.

Pediatric Population

In studies of pediatric patients with mild-to-moderate active ulcerative colitis receiving three 750 mg balsalazide disodium capsules 3 times daily (6.75 g/day) for 8 weeks, steady state was reached within 2 weeks, as observed in adult patients. Likewise, the pharmacokinetics of balsalazide, 5-ASA, and N-Ac-5-ASA were characterized by very large inter-patient variability, which is also similar to that seen in adult patients.

The pro-drug moiety, balsalazide, appeared to exhibit dose-independent (i.e., doselinear) kinetics in children, and the systemic exposure parameters (Cmax and AUC0 to 8) increased in an almost dose-proportional fashion after the 6.75 g/day versus the 2.25 g/day doses. However, the absolute magnitude of these exposure parameters was greater relative to adults. The C and AUC observed in max 0 to 8 pediatric patients were 26% and 102% greater than those observed in adult patients at the 6.75 g/day dosage level. In contrast, the systemic exposure parameters for the active metabolites, 5-ASA and N- Ac-5-ASA, in pediatric patients increased in a less than dose-proportional manner after the 6.75 g/day dose versus the 2.25 g/day dose. Additionally, the magnitude of these exposure parameters was decreased for both metabolites relative to adults. For the metabolite of key safety concern from a systemic exposure perspective, 5-ASA, the C and AUC observed in pediatric patients were max 0 to 8 67% and 64% lower than those observed in adult patients at the 6.75 g/day dosage level. Likewise, for N-Ac-5-ASA, the C and AUC observed in pediatric patients were 68% and 55% lower than max 0 to 8 those observed in adult patients at the 6.75 g/day dosage level.

All pharmacokinetic studies with balsalazide are characterized by large variability in the plasma concentration versus time profiles for balsalazide and its metabolites, thus half-life estimates of these analytes are indeterminate.

Drug Interaction Studies
In Vitro Data
In an in vitro study using human liver microsomes, balsalazide and its metabolites [5-aminosalicylic acid (5-ASA), Nacetyl-5-aminosalicylic acid (N-Ac-5-ASA), 4-aminobenzoyl-ß-alanine (4-ABA) and N-acetyl-4-aminobenzoyl-ß-alanine (N-Ac-4-ABA)] were not shown to inhibit the major CYP enzymes evaluated (CYP1A2, CYP2C9, CYP2C19, CYP2D6, and CYP3A4/5). Therefore, balsalazide and its metabolites are not expected to inhibit the metabolism of other drugs which are substrates of CYP1A2, CYP2C9, CYP2C19, CYP2D6, or CYP3A4/5.

13 NONCLINICAL TOXICOLOGY

13.1 Carcinogenesis, Mutagenesis, Impairment of Fertility

In a 24-month rat (Sprague Dawley) carcinogenicity study, oral (dietary) balsalazide disodium at doses up to 2 g/kg/day was not tumorigenic. For a 50-kg person of average height this dose represents 2.4 times the recommended human dose on a body surface area basis. Balsalazide disodium was not genotoxic in the following in vitro or in vivo tests: Ames test, human lymphocyte chromosomal aberration test, and mouse lymphoma cell (L5178Y/TK+/-) forward mutation test, or mouse micronucleus test. However, it was genotoxic in the in vitro Chinese hamster lung cell (CH V79/HGPRT) forward mutation test.

4-aminobenzoyl-β-alanine, a metabolite of balsalazide disodium, was not genotoxic in the Ames test and the mouse lymphoma cell (L5178Y/TK+/-) forward mutation test but was positive in the human lymphocyte chromosomal aberration test. N-acetyl-4-aminobenzoyl-β-alanine, a conjugated metabolite of balsalazide disodium, was not genotoxic in Ames test, the mouse lymphoma cell (L5178Y/TK+/-) forward mutation test, or the human lymphocyte chromosomal aberration test. Balsalazide disodium at oral doses up to 2 g/kg/day, 2.4 times the recommended human dose based on body surface area, was found to have no effect on fertility and reproductive performance in rats.

13.2 Animal Toxicology

Renal Toxicity

In animal studies conducted at doses up to 2000 mg/kg (approximately 21 times the recommended 6.75 g/day dose on a mg/kg basis for a 70 kg person), balsalazide demonstrated no nephrotoxic effects in rats or dogs.

Overdosage

A single oral dose of balsalazide disodium at 5 g/kg or 4-aminobenzoyl-β-alanine, a metabolite of balsalazide disodium, at 1 g/kg was non-lethal in mice and rats. No symptoms of acute toxicity were seen at these doses.

14 CLINICAL STUDIES

14.1 Adult Studies

Two randomized, double-blind studies were conducted in adults. In the first trial, 103 patients with active mild-to-moderate ulcerative colitis with sigmoidoscopy findings of friable or spontaneously bleeding mucosa were randomized and treated with balsalazide 6.75 g/day or balsalazide 2.25 g/day. The primary efficacy endpoint was reduction of rectal bleeding and improvement of at least one of the other assessed symptoms (stool frequency, patient functional assessment, abdominal pain, sigmoidoscopic grade, and physician’s global assessment [PGA]). Outcome assessment for rectal bleeding at each interim period (week 2, 4, and 8) encompassed a 4-day period (96 hours). Results demonstrated a statistically significant difference between high and low doses of balsalazide (Figure 1).

Figure 1: Percentage of Patients Improved at 8 weeks

A second study, conducted in Europe, confirmed findings of symptomatic improvement.

14.2 Pediatric Studies

A clinical trial was conducted comparing two doses (6.75 g/day and 2.25 g/day) of balsalazide disodium in 68 pediatric patients (age 5 to 17, 23 males and 45 females) with mildly to moderately active ulcerative colitis. 28/33 (85%) patients randomized to 6.75 g/day and 25/35 (71%) patients randomized to 2.25 g/day completed the study. The primary endpoint for this study was the proportion of subjects with clinical improvement (defined as a reduction of at least 3 points in the Modified Sutherland Ulcerative Colitis Activity Index [MUCAI] from baseline to 8 weeks). Fifteen (45%) patients in the balsalazide disodium 6.75 g/day group and 13 (37%) patients in the balsalazide disodium 2.25 g/day group showed this clinical improvement. In both groups, patients with higher MUCAI total scores at baseline were likely to experience greater improvement.

Rectal bleeding improved in 64% of patients treated with balsalazide disodium 6.75 g/day and 54% of patients treated with balsalazide disodium 2.25 g/day. Colonic mucosal appearance upon endoscopy improved in 61% of patients treated with balsalazide disodium 6.75 g/day and 46% of patients treated with balsalazide disodium 2.25 g/day.

16 HOW SUPPLIED/STORAGE AND HANDLING

Balsalazide Disodium Capsules, USP are available as white, opaque capsules imprinted “APO B750” in red ink.

Balsalazide Disodium Capsules, USP are supplied as follows:

NDC 50268-102-13 (10 capsules per car, 3 cards per carton)

Dispensed in Unit Dose package. For Institutional Use Only.

Storage

Store at 20º to 25ºC (68º to 77ºF); excursions permitted between 15º and 30ºC (59º and 86ºF).

See USP Controlled Room Temperature.

17 PATIENT COUNSELING INFORMATION

Renal Impairment
Inform patients that balsalazide disodium capsules may decrease their renal function, especially if they have known renal impairment or are taking nephrotoxic drugs, including NSAIDs, and periodic monitoring of renal function will be performed while they are on therapy. Advise patients to complete all blood tests ordered by their healthcare provider [see Warnings and Precautions (5.1), Drug Interactions (7.1)].

Mesalamine-Induced Acute Intolerance Syndrome and Other Hypersensitivity Reactions
Inform patients of the signs and symptoms of hypersensitivity reactions. Instruct patients to stop taking balsalazide disodium capsules and report to their healthcare provider if they experience new or worsening symptoms of Acute Intolerance Syndrome (cramping, abdominal pain, bloody diarrhea, fever, headache, and rash) or other symptoms suggestive of mesalamine-induced hypersensitivity [see Warnings and Precautions (5.2, 5.3)].

Hepatic Failure
Inform patients with known liver disease of the signs and symptoms of worsening liver function and advise them to report to their healthcare provider if they experience such signs or symptoms [see Warnings and Precautions (5.4)].

Severe Cutaneous Adverse Reactions
Inform patients of the signs and symptoms of severe cutaneous adverse reactions. Instruct patients to stop taking balsalazide disodium capsules and report to their healthcare provider at first appearance of a severe cutaneous adverse reaction or other sign of hypersensitivity [see Warnings and Precautions (5.5)].

Upper Gastrointestinal Tract Obstruction
Advise patients to contact their healthcare provider if they experience signs and symptoms of upper gastrointestinal tract obstruction [see Warnings and Precautions (5.6)].

Photosensitivity
Advise patients with pre-existing skin conditions to avoid sun exposure, wear protective clothing, and use a broad-spectrum sunscreen when outdoors [see Warnings and Precautions (5.7)].

Nephrolithiasis
Instruct patients to drink an adequate amount of fluids during treatment in order to minimize the risk of kidney stone formation and to contact their healthcare provider if they experience signs or symptoms of a kidney stone (e.g., severe side or back pain, blood in the urine) [see Warnings and Precautions (5.8)].

Blood Disorders
Inform elderly patients and those taking azathioprine or 6-mercaptopurine of the risk for blood disorders and the need for periodic monitoring of complete blood cell counts and platelet counts while on therapy. Advise patients to complete all blood tests ordered by their healthcare provider [see Drug Interactions (7.2), Use in Specific Populations (8.5)].

Administration
Instruct patients:

- Swallow balsalazide disodium capsules whole. Do not cut, break, crush or chew the capsules.
- For patients who cannot swallow intact capsules, balsalazide disodium capsules may also be administered by opening the capsule and sprinkling the capsule contents on applesauce. If the capsules are opened for sprinkling, color variation of the powder inside the capsules ranges from orange to yellow and is expected due to color variation of the active pharmaceutical ingredient.
- Place a small amount (approximately 10 mL) of applesauce into a clean container.
- Carefully open the capsules.
- Sprinkle the capsule contents on the applesauce.
- Mix the capsule contents with the applesauce. The contents may be chewed, if necessary.
- Consume the entire amount of applesauce mixture immediately. Do not store the applesauce mixture for future use.
- Teeth and/or tongue staining may occur in some patients who use balsalazide disodium capsules in sprinkle form with food.
- Drink an adequate amount of fluids.
- Take balsalazide disodium capsules without regard to meals [see Clinical Pharmacology (12.3)].
- Urine may become discolored reddish-brown while taking balsalazide disodium capsules when it comes in contact with surfaces or water treated with hypochlorite-containing bleach. If discolored urine is observed, advise patients to observe their urine flow. Report to the healthcare provider only if urine is discolored on leaving the body, before contact with any surface or water (e.g., in the toilet).

Manufactured For:
AvKARE
Pulaski, TN 38478

Mfg. Rev. 12/23
AV Rev. 10/25(M)
AvPAK